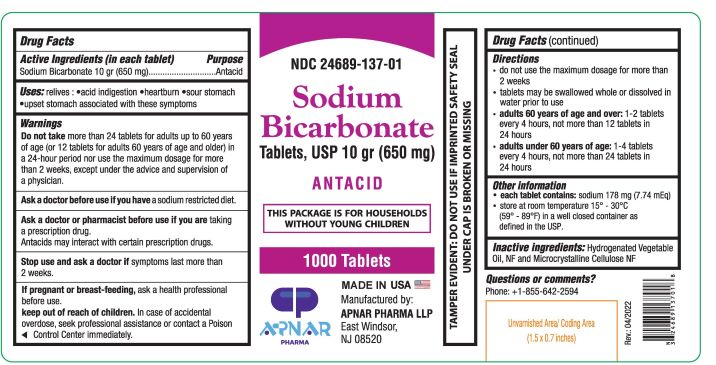 DRUG LABEL: Sodium Bicarbonate
NDC: 24689-137 | Form: TABLET
Manufacturer: APNAR PHARMA LP
Category: otc | Type: HUMAN OTC DRUG LABEL
Date: 20231021

ACTIVE INGREDIENTS: SODIUM BICARBONATE 650 mg/1 1
INACTIVE INGREDIENTS: MICROCRYSTALLINE CELLULOSE; CORN OIL

Sodium Bicarbonate Tablets, USP 10gr (650mg)

Drug Facts
Active ingredients (in each tablet)

Sodium Bicarbonate 10 gr (650mg)

PURPOSE

Antacid

INDICATIONS AND USAGE

Uses: relieves • acid indigestion • heartburn • sour stomach • upset stomach associated with these symptoms

Warnings

Do not take more than 24 tablets for adults up to 60 years of age (or 12 tablets for adults 60 years of age and older) in a 24-hour period nor use the maximum dosage for more than 2 weeks, except under the advice and supervision of a physician.

Ask a doctor beforeuse if you have a sodium restricted diet.

Ask a doctor or pharmacist before use if you are taking a prescription drug. Antacids may interact with certain prescription drugs.

Stop use and ask a doctor if symptoms last more than 2 weeks

If pregnant or breast-feeding, ask a health professional before use.

Keep out of reach of children.

In case of accidental overdose, seek professional assistance or contact a Poison Control Center immediately.

Directions

- do not use the maximum dosage for more than 2 weeks
- tablets may be swallowed whole or dissolved in water prior to use
- adults 60 years of age and over: 1-2 tablets every 4 hours, not more than 12 tablets in 24 hours
- adults under 60 years of age: 1-4 tablets every 4 hours, not more than 24 tablets in 24 hours

Other Information:

- each tablet contains: sodium 178 mg (7.74 mEq)
- store at room temperature 15°-30°C (59°-86°F) in a well closed container as defined in the USP.

INACTIVE INGREDIENT

Inactive Ingredients: Microcrystalline cellulose NF, Hydrogenated Vegetable oil NF

Questions or Comments?

Phone +1-855-642-2594

Rev.: 04/2022

MADE IN USA

Manufactured by:

APNAR PHARMA LLP

East Windsor

NJ 08520

BOXED WARNING

TAMPER EVIDENT: DO NOT USE IF IMPRINTED SAFETY SEAL UNDER CAP IS BROKEN OR MISSING

Sodium Bicarbonate Tablets,USP 10gr (650mg)-1000 Tablets

NDC : 24689-137-01

Sodium
Bicarbonate 10 gr TABLETS, USP
Antacid

THIS PACKAGE FOR HOUSEHOLDS WITHOUT YOUNG CHILDREN.

1000 Tablets